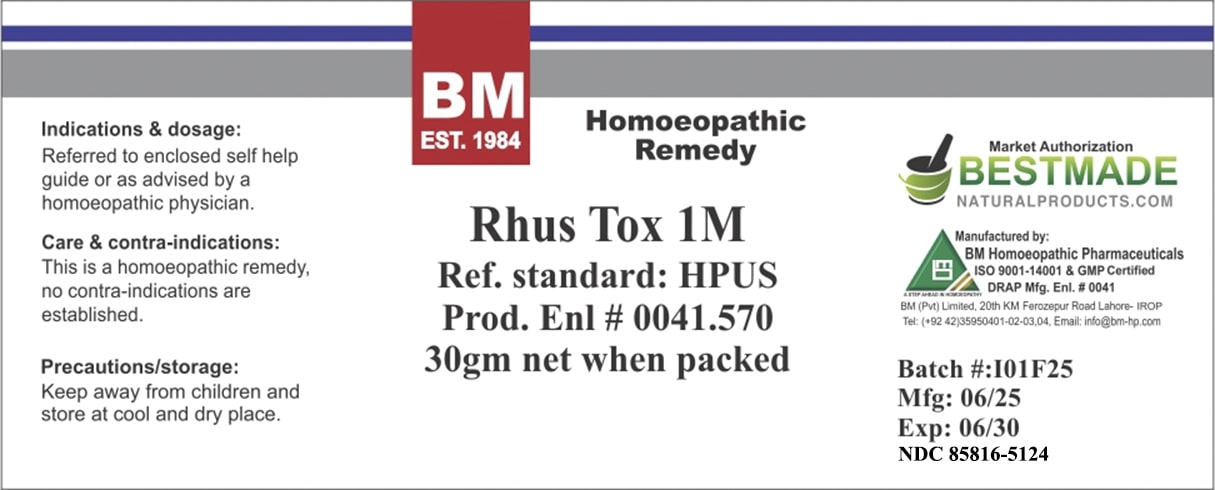 DRUG LABEL: BM Rhus Tox
NDC: 85816-5124 | Form: LIQUID
Manufacturer: BM Private Limited
Category: homeopathic | Type: HUMAN OTC DRUG LABEL
Date: 20250701

ACTIVE INGREDIENTS: TOXICODENDRON PUBESCENS LEAF 1000 [hp_C]/1 mL
INACTIVE INGREDIENTS: ALCOHOL 0.9 mL/1 mL

BM Rhus Tox 1M

INACTIVE INGREDIENT

ALCOHOL

ACTIVE INGREDIENT

RHUS TOXICODENDRON

Indications & dosage: As advised by a homoeopathic physician.

PURPOSE

Indications & dosage: As advised by a homoeopathic physician.

Indications & dosage: As advised by a homoeopathic physician.

CONTRAINDICATIONS

Care & contra-indications: This is a homoeopathic product, no contra-indications are established.

WARNINGS

Precautions/storage: Keep away from children and store at cool and dry place.

STORAGE AND HANDLING

Precautions/storage: Keep away from children and store at cool and dry place.

KEEP OUT OF REACH OF CHILDREN

Precautions/storage: Keep away from children and store at cool and dry place.

Entire package label